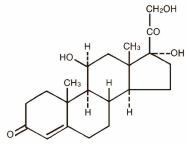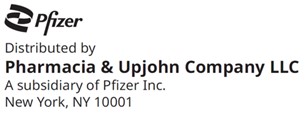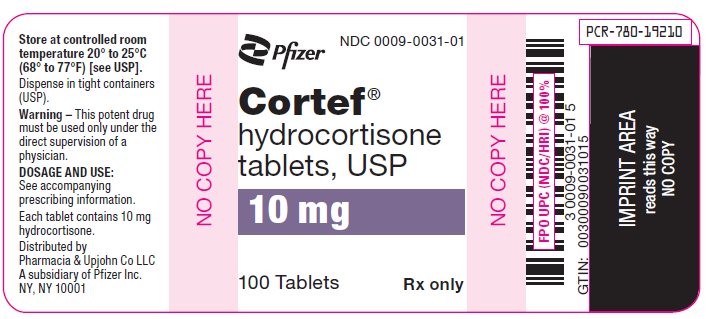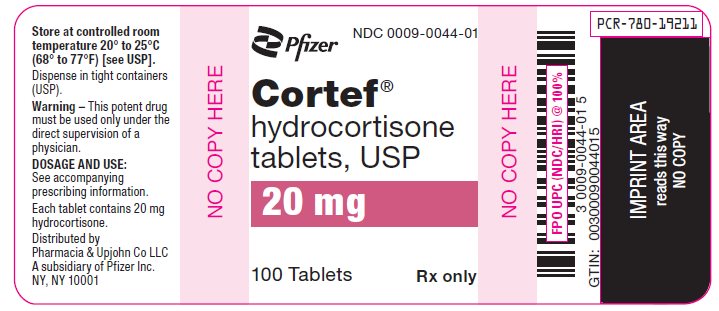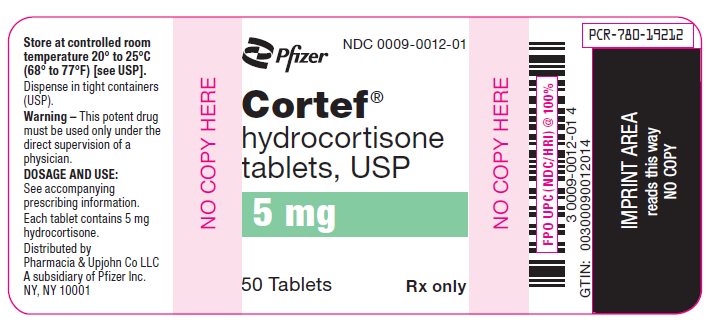 DRUG LABEL: CORTEF
NDC: 0009-0012 | Form: TABLET
Manufacturer: Pharmacia & Upjohn Company LLC
Category: prescription | Type: HUMAN PRESCRIPTION DRUG LABEL
Date: 20250217

ACTIVE INGREDIENTS: HYDROCORTISONE 5 mg/1 1
INACTIVE INGREDIENTS: CALCIUM STEARATE; STARCH, CORN; LACTOSE, UNSPECIFIED FORM; MINERAL OIL; SORBIC ACID; SUCROSE

Cortef®
hydrocortisone
tablets, USP

DESCRIPTION

CORTEF Tablets contain hydrocortisone which is a glucocorticoid. Glucocorticoids are adrenocortical steroids, both naturally occurring and synthetic, which are readily absorbed from the gastrointestinal tract. Hydrocortisone USP is white to practically white, odorless, crystalline powder with a melting point of about 215° C. It is very slightly soluble in water and in ether; sparingly soluble in acetone and in alcohol; slightly soluble in chloroform.

The chemical name for hydrocortisone is pregn-4-ene-3,20-dione,11,17,21-trihydroxy-, (11β)-. Its molecular weight is 362.46 and the structural formula is as outlined below.

CORTEF Tablets are available for oral administration in three strengths: each tablet contains either 5 mg, 10 mg, or 20 mg of hydrocortisone. Inactive ingredients: calcium stearate, corn starch, lactose, mineral oil, sorbic acid, sucrose.

ACTIONS

Naturally occurring glucocorticoids (hydrocortisone and cortisone), which also have salt-retaining properties, are used as replacement therapy in adrenocortical deficiency states. Their synthetic analogs are primarily used for their potent anti-inflammatory effects in disorders of many organ systems.

Glucocorticoids cause profound and varied metabolic effects. In addition, they modify the body's immune responses to diverse stimuli.

INDICATIONS AND USAGE

CORTEF Tablets are indicated in the following conditions.

1. Endocrine Disorders

Primary or secondary adrenocortical insufficiency (hydrocortisone or cortisone is the first choice; synthetic analogs may be used in conjunction with mineralocorticoids where applicable; in infancy mineralocorticoid supplementation is of particular importance)
Congenital adrenal hyperplasia
Non suppurative thyroiditis
Hypercalcemia associated with cancer

2. Rheumatic Disorders

As adjunctive therapy for short-term administration (to tide the patient over an acute episode or exacerbation) in:

Psoriatic arthritis
Rheumatoid arthritis, including juvenile rheumatoid arthritis (selected cases may require low-dose maintenance therapy)
Ankylosing spondylitis
Acute and subacute bursitis
Acute nonspecific tenosynovitis
Acute gouty arthritis
Post-traumatic osteoarthritis
Synovitis of osteoarthritis
Epicondylitis

3. Collagen Diseases

During an exacerbation or as maintenance therapy in selected cases of:

Systemic lupus erythematosus
Systemic dermatomyositis (polymyositis)
Acute rheumatic carditis

4. Dermatologic Diseases

Pemphigus
Bullous dermatitis herpetiformis
Severe erythema multiforme (Stevens-Johnson syndrome)
Exfoliative dermatitis
Mycosis fungoides
Severe psoriasis
Severe seborrheic dermatitis

5. Allergic States

Control of severe or incapacitating allergic conditions intractable to adequate trials of conventional treatment:

Seasonal or perennial allergic rhinitis
Serum sickness
Bronchial asthma
Contact dermatitis
Atopic dermatitis
Drug hypersensitivity reactions

6. Ophthalmic Diseases

Severe acute and chronic allergic and inflammatory processes involving the eye and its adnexa such as:

Allergic conjunctivitis
Keratitis
Allergic corneal marginal ulcers
Herpes zoster ophthalmicus
Iritis and iridocyclitis
Chorioretinitis
Anterior segment inflammation
Diffuse posterior uveitis and choroiditis
Optic neuritis
Sympathetic ophthalmia

7. Respiratory Diseases

Symptomatic sarcoidosis
Loeffler's syndrome not manageable by other means
Berylliosis
Fulminating or disseminated pulmonary tuberculosis when used concurrently with appropriate antituberculous chemotherapy
Aspiration pneumonitis

8. Hematologic Disorders

Idiopathic thrombocytopenic purpura in adults
Secondary thrombocytopenia in adults
Acquired (autoimmune) hemolytic anemia
Erythroblastopenia (RBC anemia)
Congenital (erythroid) hypoplastic anemia

9. Neoplastic Diseases

For palliative management of:

Leukemias and lymphomas in adults
Acute leukemia of childhood

10. Edematous States

To induce a diuresis or remission of proteinuria in the nephrotic syndrome, without uremia, of the idiopathic type or that due to lupus erythematosus.

11. Gastrointestinal Diseases

To tide the patient over a critical period of the disease in:

Ulcerative colitis
Regional enteritis

12. Miscellaneous

Tuberculous meningitis with subarachnoid block or impending block when used concurrently with appropriate antituberculous chemotherapy
Trichinosis with neurologic or myocardial involvement

CONTRAINDICATIONS

Systemic fungal infections and known hypersensitivity to components

WARNINGS

In patients on corticosteroid therapy subjected to unusual stress, increased dosage of rapidly acting corticosteroids before, during, and after the stressful situation is indicated.

Immunosuppression and Increased Risk of Infection

Corticosteroids, including CORTEF, suppress the immune system and increase the risk of infection with any pathogen, including viral, bacterial, fungal, protozoan, or helminthic pathogens. Corticosteroids can:

- Reduce resistance to new infections
- Exacerbate existing infections
- Increase the risk of disseminated infections
- Increase the risk of reactivation or exacerbation of latent infections
- Mask some signs of infection

Corticosteroid-associated infections can be mild but can be severe and at times fatal. The rate of infectious complications increases with increasing corticosteroid dosages.

Monitor for the development of infection and consider CORTEF withdrawal or dosage reduction as needed.

Tuberculosis

If CORTEF is used to treat a condition in patients with latent tuberculosis or tuberculin reactivity, reactivation of tuberculosis may occur. Closely monitor such patients for reactivation. During prolonged CORTEF therapy, patients with latent tuberculosis or tuberculin reactivity should receive chemoprophylaxis.

Varicella Zoster and Measles Viral Infections

Varicella and measles can have a serious or even fatal course in non-immune patients taking corticosteroids, including CORTEF. In corticosteroid-treated patients who have not had these diseases or are non-immune, particular care should be taken to avoid exposure to varicella and measles:

- If a CORTEF-treated patient is exposed to varicella, prophylaxis with varicella zoster immune globulin may be indicated. If varicella develops, treatment with antiviral agents may be considered.
- If a CORTEF-treated patient is exposed to measles, prophylaxis with immunoglobulin may be indicated.

Hepatitis B Virus Reactivation

Hepatitis B virus reactivation can occur in patients who are hepatitis B carriers treated with immunosuppressive dosages of corticosteroids, including CORTEF. Reactivation can also occur infrequently in corticosteroid-treated patients who appear to have resolved hepatitis B infection.

Screen patients for hepatitis B infection before initiating immunosuppressive (e.g., prolonged) treatment with CORTEF. For patients who show evidence of hepatitis B infection, recommend consultation with physicians with expertise in managing hepatitis B regarding monitoring and consideration for hepatitis B antiviral therapy.

Fungal Infections

Corticosteroids, including CORTEF, may exacerbate systemic fungal infections; therefore, avoid CORTEF use in the presence of such infections unless CORTEF is needed to control drug reactions. For patients on chronic CORTEF therapy who develop systemic fungal infections, CORTEF withdrawal or dosage reduction is recommended.

Amebiasis

Corticosteroids, including CORTEF, may activate latent amebiasis. Therefore, it is recommended that latent amebiasis or active amebiasis be ruled out before initiating CORTEF in patients who have spent time in the tropics or patients with unexplained diarrhea.

Strongyloides Infestation

Corticosteroids, including CORTEF, should be used with great care in patients with known or suspected Strongyloides (threadworm) infestation. In such patients, corticosteroid-induced immunosuppression may lead to Strongyloides hyperinfection and dissemination with widespread larval migration, often accompanied by severe enterocolitis and potentially fatal gram-negative septicemia.

Cerebral Malaria

Avoid corticosteroids, including CORTEF, in patients with cerebral malaria.

Ophthalmic Effects

Prolonged use of corticosteroids may produce posterior subcapsular cataracts, glaucoma with possible damage to the optic nerves, and may enhance the establishment of secondary ocular infections due to fungi or viruses.

Kaposi’s Sarcoma

Kaposi’s sarcoma has been reported to occur in patients receiving corticosteroid therapy, most often for chronic conditions. Discontinuation of corticosteroids may result in clinical improvement of Kaposi’s sarcoma.

Hypertension, Volume Overload, and Hypokalemia

Average and large doses of hydrocortisone or cortisone can cause elevation of blood pressure, salt and water retention, and increased excretion of potassium. These effects are less likely to occur with the synthetic derivatives except when used in large doses. Dietary salt restriction and potassium supplementation may be necessary. All corticosteroids increase calcium excretion.

Vaccinations

Administration of live or live, attenuated vaccines is contraindicated in patients receiving immunosuppressive doses of corticosteroids. Killed or inactivated vaccines may be administered to patients receiving immunosuppressive doses of corticosteroids; however, the response to such vaccines may be diminished. Indicated immunization procedures may be undertaken in patients receiving nonimmunosuppressive doses of corticosteroids.

Usage in Pregnancy

Since adequate human reproduction studies have not been done with corticosteroids, the use of these drugs in pregnancy, nursing mothers or women of child bearing potential requires that the possible benefits of the drug be weighed against the potential hazards to the mother and embryo or fetus. Infants born of mothers who have received substantial doses of corticosteroids during pregnancy, should be carefully observed for signs of hypoadrenalism.

Corticosteroids have been shown to impair fertility in male rats.

PRECAUTIONS

General Precautions

Drug-induced secondary adrenocortical insufficiency may be minimized by gradual reduction of dosage. This type of relative insufficiency may persist for months after discontinuation of therapy; therefore, in any situation of stress occurring during that period, hormone therapy should be reinstituted.

There is an enhanced effect of corticosteroids on patients with hypothyroidism and in those with cirrhosis.

Corticosteroids should be used cautiously in patients with ocular herpes simplex because of possible corneal perforation.

The lowest possible dose of corticosteroid should be used to control the condition under treatment, and when reduction in dosage is possible, the reduction should be gradual.

Psychic derangements may appear when corticosteroids are used, ranging from euphoria, insomnia, mood swings, personality changes, and severe depression, to frank psychotic manifestations. Also, existing emotional instability or psychotic tendencies may be aggravated by corticosteroids.

Steroids should be used with caution in nonspecific ulcerative colitis, if there is a probability of impending perforation, abscess or other pyogenic infection; diverticulitis; fresh intestinal anastomoses; active or latent peptic ulcer; renal insufficiency; hypertension; osteoporosis; and myasthenia gravis.

Growth and development of infants and children on prolonged corticosteroid therapy should be carefully observed.

Since complications of treatment with glucocorticoids are dependent on the size of the dose and the duration of treatment, a risk/benefit decision must be made in each individual case as to dose and duration of treatment and as to whether daily or intermittent therapy should be used.

Pheochromocytoma crisis, which can be fatal, has been reported after administration of systemic corticosteroids. In patients with suspected pheochromocytoma, consider the risk of pheochromocytoma crisis prior to administering corticosteroids.

In post marketing experience tumor lysis syndrome (TLS) has been reported in patients with malignancies, including hematological malignancies and solid tumors, following the use of systemic corticosteroids alone or in combination with other chemotherapeutic agents. Patients at high risk of TLS, such as patients with tumors that have a high proliferative rate, high tumor burden and high sensitivity to cytotoxic agents, should be monitored closely and appropriate precautions should be taken.

Drug Interactions

The pharmacokinetic interactions listed below are potentially clinically important. Drugs that induce hepatic enzymes such as phenobarbital, phenytoin and rifampin may increase the clearance of corticosteroids and may require increases in corticosteroid dose to achieve the desired response. Drugs such as troleandomycin and ketoconazole may inhibit the metabolism of corticosteroids and thus decrease their clearance. Therefore, the dose of corticosteroid should be titrated to avoid steroid toxicity. Corticosteroids may increase the clearance of chronic high dose aspirin. This could lead to decreased salicylate serum levels or increase the risk of salicylate toxicity when corticosteroid is withdrawn. Aspirin should be used cautiously in conjunction with corticosteroids in patients suffering from hypoprothrombinemia. The effect of corticosteroids on oral anticoagulants is variable. There are reports of enhanced as well as diminished effects of anticoagulants when given concurrently with corticosteroids. Therefore, coagulation indices should be monitored to maintain the desired anticoagulant effect.

Information for the Patient

Persons who are on immunosuppressant doses of corticosteroids should be warned to avoid exposure to chicken pox or measles. Patients should also be advised that if they are exposed, medical advice should be sought without delay.

ADVERSE REACTIONS

Fluid and Electrolyte Disturbances

Sodium retention
Fluid retention
Congestive heart failure in susceptible patients
Potassium loss
Hypokalemic alkalosis
Hypertension

Musculoskeletal

Muscle weakness
Steroid myopathy
Loss of muscle mass
Osteoporosis
Tendon rupture, particularly of the Achilles tendon
Vertebral compression fractures
Aseptic necrosis of femoral and humeral heads
Pathologic fracture of long bones

Gastrointestinal

Peptic ulcer with possible perforation and hemorrhage
Pancreatitis
Abdominal distention
Ulcerative esophagitis
Increases in alanine transaminase (ALT, SGPT), aspartate transaminase (AST, SGOT) and alkaline phosphatase have been observed following corticosteroid treatment. These changes are usually small, not associated with any clinical syndrome and are reversible upon discontinuation.

Dermatologic

Impaired wound healing
Thin fragile skin
Petechiae and ecchymoses
Facial erythema
Increased sweating
May suppress reactions to skin tests

Neurological

Increased intracranial pressure with papilledema (pseudotumor cerebri) usually after treatment
Convulsions
Vertigo
Headache
Epidural lipomatosis

Endocrine

Development of Cushingoid state
Suppression of growth in children
Secondary adrenocortical and pituitary unresponsiveness, particularly in times of stress, as in trauma, surgery or illness
Menstrual irregularities
Decreased carbohydrate tolerance
Manifestations of latent diabetes mellitus
Increased requirements for insulin or oral hypoglycemic agents in diabetics

Ophthalmic

Central serous chorioretinopathy
Posterior subcapsular cataracts
Increased intraocular pressure
Glaucoma
Exophthalmos

Metabolic

Negative nitrogen balance due to protein catabolism

Blood and lymphatic system disorders

Leukocytosis

DOSAGE AND ADMINISTRATION

The initial dosage of CORTEF Tablets may vary from 20 mg to 240 mg of hydrocortisone per day depending on the specific disease entity being treated. In situations of less severity lower doses will generally suffice while in selected patients higher initial doses may be required. The initial dosage should be maintained or adjusted until a satisfactory response is noted. If after a reasonable period of time there is a lack of satisfactory clinical response, CORTEF should be discontinued and the patient transferred to other appropriate therapy. IT SHOULD BE EMPHASIZED THAT DOSAGE REQUIREMENTS ARE VARIABLE AND MUST BE INDIVIDUALIZED ON THE BASIS OF THE DISEASE UNDER TREATMENT AND THE RESPONSE OF THE PATIENT. After a favorable response is noted, the proper maintenance dosage should be determined by decreasing the initial drug dosage in small decrements at appropriate time intervals until the lowest dosage which will maintain an adequate clinical response is reached. It should be kept in mind that constant monitoring is needed in regard to drug dosage. Included in the situations which may make dosage adjustments necessary are changes in clinical status secondary to remissions or exacerbations in the disease process, the patient's individual drug responsiveness, and the effect of patient exposure to stressful situations not directly related to the disease entity under treatment; in this latter situation it may be necessary to increase the dosage of CORTEF for a period of time consistent with the patient's condition. If after long-term therapy the drug is to be stopped, it is recommended that it be withdrawn gradually, rather than abruptly.

HOW SUPPLIED

CORTEF Tablets are available in the following strengths and package sizes:

5 mg (white, round, scored, imprinted CORTEF 5)
Bottles of 50 NDC 0009-0012-01

10 mg (white, round, scored, imprinted CORTEF 10)
Bottles of 100 NDC 0009-0031-01

20 mg (white, round, scored, imprinted CORTEF 20)
Bottles of 100 NDC 0009-0044-01

Store at controlled room temperature 20° to 25°C (68° to 77°F) [see USP].

REFERENCES

^1Fekety R. Infections associated with corticosteroids and immunosuppressive therapy. In: Gorbach SL, Bartlett JG, Blacklow NR, eds. Infectious Diseases. Philadelphia: WB Saunders Company 1992:1050–1.

^2Stuck AE, Minder CE, Frey FJ. Risk of infectious complications in patients taking glucocorticoids. Rev Infect Dis 1989:11(6):954–63.

Rx only

LAB-0117-7.0
Revised February 2024

PRINCIPAL DISPLAY PANEL - 5 mg Tablet Bottle Label

NDC 0009-0012-01

Pfizer

Cortef®
hydrocortisone
tablets, USP

5 mg

50 Tablets
Rx only

PRINCIPAL DISPLAY PANEL - 10 mg Tablet Bottle Label

NDC 0009-0031-01

Pfizer

Cortef®
hydrocortisone
tablets, USP

10 mg

100 Tablets
Rx only

PRINCIPAL DISPLAY PANEL - 20 mg Tablet Bottle Label

NDC 0009-0044-01

Pfizer

Cortef®
hydrocortisone
tablets, USP

20 mg

100 Tablets
Rx only